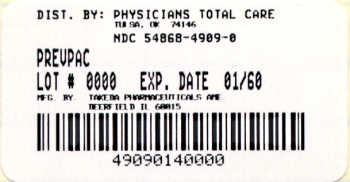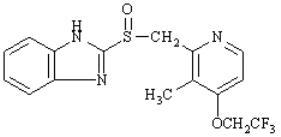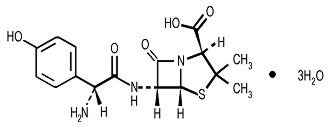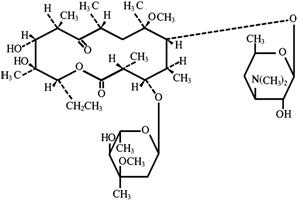 DRUG LABEL: PREVPAC
NDC: 54868-4909 | Form: KIT | Route: ORAL
Manufacturer: Physicians Total Care, Inc.
Category: prescription | Type: HUMAN PRESCRIPTION DRUG LABEL
Date: 20100315

ACTIVE INGREDIENTS: LANSOPRAZOLE 30 mg/1 1; AMOXICILLIN 500 mg/1 1; CLARITHROMYCIN 500 mg/1 1
INACTIVE INGREDIENTS: SUCROSE; HYDROXYPROPYL CELLULOSE, LOW SUBSTITUTED; MAGNESIUM CARBONATE; TALC; POLYETHYLENE GLYCOL; TITANIUM DIOXIDE; POLYSORBATE 80; HYDROXYPROPYL CELLULOSE; SILICON DIOXIDE; D&C RED NO. 28; FD&C BLUE NO. 1; FD&C RED NO. 40; METHACRYLIC ACID - ETHYL ACRYLATE COPOLYMER (1:1) TYPE A; STARCH, CORN; FERRIC OXIDE YELLOW; TITANIUM DIOXIDE; GELATIN; FERROSOFERRIC OXIDE; CELLULOSE, MICROCRYSTALLINE; MAGNESIUM STEARATE; HYPROMELLOSES; HYDROXYPROPYL CELLULOSE; SILICON DIOXIDE; CROSCARMELLOSE SODIUM; D&C YELLOW NO. 10; MAGNESIUM STEARATE; CELLULOSE, MICROCRYSTALLINE; POVIDONE; PROPYLENE GLYCOL; SORBIC ACID; SORBITAN MONOOLEATE; TITANIUM DIOXIDE; VANILLIN

PREVPAC®
(lansoprazole 30 mg capsules, amoxicillin 500 mg capsules, USP, and clarithromycin 500 mg tablets, USP)

To reduce the development of drug-resistant bacteria and maintain the effectiveness of PREVPAC and other antibacterial drugs, PREVPAC should be used only to treat or prevent infections that are proven or strongly suspected to be caused by bacteria.

THESE PRODUCTS ARE INTENDED ONLY FOR USE AS DESCRIBED. The individual products contained in this package should not be used alone or in combination for other purposes. The information described in this labeling concerns only the use of these products as indicated in this daily administration pack. For information on use of the individual components when dispensed as individual medications outside this combined use for treating Helicobacter pylori (H. pylori), please see the package inserts for each individual product.

DESCRIPTION

PREVPAC consists of a daily administration card containing two PREVACID 30 mg capsules, four amoxicillin 500-mg capsules, USP, and two clarithromycin 500 mg tablets, USP, for oral administration.

PREVACID® (lansoprazole) Delayed-Release Capsules

The active ingredient in PREVACID delayed release capsules is lansoprazole, a substituted benzimidazole, 2-[[[3-methyl-4-(2,2,2-trifluoroethoxy)-2-pyridyl] methyl] sulfinyl] benzimidazole, a compound that inhibits gastric acid secretion. Its empirical formula is C16H14F3N3O2S with a molecular weight of 369.37. PREVACID has the following structure:

Lansoprazole is a white to brownish-white odorless crystalline powder which melts with decomposition at approximately 166°C. Lansoprazole is freely soluble in dimethylformamide; soluble in methanol; sparingly soluble in ethanol; slightly soluble in ethyl acetate, dichloromethane and acetonitrile; very slightly soluble in ether; and practically insoluble in hexane and water.

Each delayed-release capsule contains enteric-coated granules consisting of 30 mg of lansoprazole (active ingredient) and the following inactive ingredients: sugar sphere, sucrose, methacrylic acid copolymer, low substituted hydroxypropyl cellulose, starch, magnesium carbonate, talc, polyethylene glycol, titanium dioxide, polysorbate 80, hydroxypropyl cellulose, colloidal silicon dioxide, D&C Red No. 28, FD&C Blue No. 1, and FD&C Red No. 40.

Amoxicillin Capsules, USP

Amoxicillin is a semi synthetic antibiotic, an analogue of ampicillin, with a broad spectrum of bactericidal activity against many gram-positive and gram-negative microorganisms. Chemically it is (2S, 5R, 6R)-6-[(R)-(-)-2-amino-2-(p-hydroxyphenyl)acetamido]-3,3-dimethyl-7-oxo-4-thia-1-azabicyclo[3.2.0] heptane-2-carboxylic acid trihydrate. Its empirical formula is C16H19N3O5S • 3H2O with a molecular weight of 419.45. Amoxicillin has the following structure:

Amoxicillin capsules are intended for oral administration. Each yellow opaque capsule contains amoxicillin trihydrate equivalent to 500 mg of amoxicillin.

Inactive ingredients: Capsule shells - yellow ferric oxide, titanium dioxide, gelatin, black ferric oxide; Capsule contents – cellulose microcrystalline and magnesium stearate. Meets USP Dissolution Test 2.

BIAXIN® Filmtab® (clarithromycin tablets, USP)

Clarithromycin is a semi-synthetic macrolide antibiotic. Chemically, it is 6-0-methylerythromycin. The molecular formula is C38H69NO13, and the molecular weight is 747.96. Clarithromycin has the following structure:

Clarithromycin is a white to off-white crystalline powder. It is soluble in acetone, slightly soluble in methanol, ethanol, and acetonitrile, and practically insoluble in water. Each yellow oval film-coated immediate-release tablet contains 500 mg of clarithromycin and the following inactive ingredients: hypromellose, hydroxypropyl cellulose, colloidal silicon dioxide, croscarmellose sodium, D&C Yellow No. 10, magnesium stearate, microcrystalline cellulose, povidone, propylene glycol, sorbic acid, sorbitan monooleate, titanium dioxide, and vanillin.

CLINICAL PHARMACOLOGY

Pharmacokinetics

Pharmacokinetics when all three of the PREVPAC components (PREVACID capsules, amoxicillin capsules, clarithromycin tablets) were coadministered has not been studied. Studies have shown no clinically significant interactions of PREVACID and amoxicillin or PREVACID and clarithromycin when administered together. There is no information about the gastric mucosal concentrations of PREVACID, amoxicillin and clarithromycin after administration of these agents concomitantly. The systemic pharmacokinetic information presented below is based on studies in which each product was administered alone.

PREVACID

PREVACID capsules contain an enteric-coated granule formulation of lansoprazole. Absorption of lansoprazole begins only after the granules leave the stomach. Absorption is rapid, with mean peak plasma levels of lansoprazole occurring after approximately 1.7 hours. After a single-dose administration of 15 mg to 60 mg of oral lansoprazole, the peak plasma concentrations (Cmax) of lansoprazole and the area under the plasma concentration curves (AUCs) of lansoprazole were approximately proportional to the administered dose. Lansoprazole does not accumulate and its pharmacokinetics are unaltered by multiple dosing.

Absorption

The absorption of lansoprazole is rapid, with the mean Cmax occurring approximately 1.7 hours after oral dosing, and the absolute bioavailability is over 80%. In healthy subjects, the mean (± SD) plasma half-life was 1.5 (± 1.0) hours. Both the Cmax and AUC are diminished by about 50 to 70% if lansoprazole is given 30 minutes after food, compared to the fasting condition. There is no significant food effect if lansoprazole is given before meals.

Distribution

Lansoprazole is 97% bound to plasma proteins. Plasma protein binding is consistent over the concentration range of 0.05 to 5.0 mcg/mL.

Metabolism

Lansoprazole is extensively metabolized in the liver. Two metabolites have been identified in measurable quantities in plasma (the hydroxylated sulfinyl and sulfone derivatives of lansoprazole). These metabolites have very little or no antisecretory activity. Lansoprazole is thought to be transformed into two active species which inhibit acid secretion by blocking the proton pump [(H^+,K^+)-ATPase enzyme system] at the secretory surface of the gastric parietal cell. The two active species are not present in the systemic circulation. The plasma elimination half-life of lansoprazole is less than 2 hours while the acid inhibitory effect lasts more than 24 hours. Therefore, the plasma elimination half-life of lansoprazole does not reflect its duration of suppression of gastric acid secretion.

Elimination

Following single-dose oral administration of PREVACID, virtually no unchanged lansoprazole was excreted in the urine. In one study, after a single oral dose of ^14C-lansoprazole, approximately one-third of the administered radiation was excreted in the urine and two-thirds was recovered in the feces. This implies a significant biliary excretion of the lansoprazole metabolites.

Amoxicillin

Amoxicillin is stable in the presence of gastric acid and may be given without regard to meals. It is rapidly absorbed after oral administration. It diffuses readily into most body tissues and fluids, with the exception of brain and spinal fluid, except when meninges are inflamed. The half-life of amoxicillin is 61.3 minutes. Most of the amoxicillin is excreted unchanged in the urine; its excretion can be delayed by concurrent administration of probenecid. In blood serum, amoxicillin is approximately 20% protein-bound.

Orally administered doses of 500 mg amoxicillin capsules result in average peak blood levels 1 to 2 hours after administration in the range of 5.5 mcg/mL to 7.5 mcg/mL.

Detectable serum levels are observed up to 8 hours after an orally administered dose of amoxicillin. Approximately 60% of an orally administered dose of amoxicillin is excreted in the urine within 6 to 8 hours.

Clarithromycin

Clarithromycin is rapidly absorbed from the gastrointestinal tract after oral administration. The absolute bioavailability of 250 mg clarithromycin tablets was approximately 50%. For a single 500 mg dose of clarithromycin, food slightly delays the onset of clarithromycin absorption, increasing the peak time from approximately 2 to 2.5 hours. Food also increases the clarithromycin peak plasma concentration by about 24%, but does not affect the extent of clarithromycin bioavailability. Food does not affect the onset of formation of the antimicrobially active metabolite, 14-OH clarithromycin or its peak plasma concentration but does slightly decrease the extent of metabolite formation, indicated by an 11% decrease in area under the plasma concentration-time curve (AUC). Therefore, clarithromycin tablets may be given without regard to food.

In nonfasting healthy human subjects (males and females), peak plasma concentrations were attained within 2 to 3 hours after oral dosing. Steady-state peak plasma clarithromycin concentrations were attained within 3 days and were approximately 3 to 4 mcg/mL with a 500 mg dose administered every 8 to 12 hours. The elimination half-life of clarithromycin was 5 to 7 hours with 500 mg administered every 8 to 12 hours. The nonlinearity of clarithromycin pharmacokinetics is slight at the recommended dose of 500 mg administered every 8 to 12 hours. With a 500 mg every 8 to 12 hours dosing, the peak steady-state concentration of 14-OH clarithromycin is up to 1 mcg/mL, and its elimination half-life is about 7 to 9 hours. The steady-state concentration of this metabolite is generally attained within 3 to 4 days.

After a 500 mg tablet every 12 hours, the urinary excretion of clarithromycin is approximately 30%. The renal clearance of clarithromycin approximates the normal glomerular filtration rate. The major metabolite found in urine is 14-OH clarithromycin, which accounts for an additional 10% to 15% of the dose with a 500 mg tablet administered every 12 hours.

The steady-state concentrations of clarithromycin in subjects with impaired hepatic function did not differ from those in normal subjects; however, the 14-OH clarithromycin concentrations were lower in the hepatically impaired subjects. The decreased formation of 14-OH clarithromycin was at least partially offset by an increase in renal clearance of clarithromycin in the subjects with impaired hepatic function when compared to healthy subjects.

The pharmacokinetics of clarithromycin was also altered in subjects with impaired renal function (see PRECAUTIONS and DOSAGE AND ADMINISTRATION).

Special Populations

Geriatric Use

The clearance of lansoprazole is decreased in the elderly, with elimination half-life increased approximately 50% to 100%. Because the mean half-life in the elderly remains between 1.9 to 2.9 hours, repeated once daily dosing does not result in accumulation of lansoprazole. Peak plasma levels were not increased in the elderly.

Renal Impairment

In patients with severe renal impairment, plasma protein binding decreased by 1.0% to 1.5% after administration of 60 mg of lansoprazole. Patients with renal impairment had a shortened elimination half-life and decreased total AUC (free and bound). The AUC for free lansoprazole in plasma, however, was not related to the degree of renal impairment; and the Cmax and Tmax (time to reach the maximum concentration) were not different than the Cmax and Tmax from subjects with normal renal function.

Hepatic Impairment

In patients with various degrees of chronic hepatic impairment, the mean plasma half-life of lansoprazole was prolonged from 1.5 hours to 3.2 to 7.2 hours. An increase in the mean AUC of up to 500% was observed at steady state in hepatically-impaired patients compared to healthy subjects. Consider dose reduction in patients with severe hepatic impairment.

Gender

In a study comparing 12 male and 6 female human subjects who received lansoprazole, no gender differences were found in pharmacokinetics and intragastric pH results (see PRECAUTIONS, PREVACID, Use in Women).

Race

The pooled pharmacokinetic parameters of PREVACID from twelve U.S. Phase I studies (N=513) were compared to the mean pharmacokinetic parameters from two Asian studies (N=20). The mean AUCs of PREVACID in Asian subjects were approximately twice those seen in pooled U.S. data; however, the inter-individual variability was high. The Cmax values were comparable.

Microbiology

Lansoprazole, clarithromycin and/or amoxicillin have been shown to be active against most strains of Helicobacter pylori in vitro and in clinical infections as described in the INDICATIONS AND USAGE section.

Pretreatment Resistance

Clarithromycin pretreatment resistance rates (≥2.0 mcg/mL) were 9.5% (91/960) by E-test and 11.3% (12/106) by agar dilution in the dual and triple therapy clinical trials (M93-125, M93-130, M93-131, M95-392, and M95-399).

Amoxicillin pretreatment susceptible isolates (≤0.25 mcg/mL) occurred in 97.8% (936/957) and 98.0% (98/100) of the patients in the dual and triple therapy clinical trials by E-test and agar dilution, respectively. Twenty-one of 957 patients (2.2%) by E-test, and 2 of 100 patients (2.0%) by agar dilution, had amoxicillin pretreatment MICs of greater than 0.25 mcg/mL. One patient on the 14-day triple therapy regimen had an unconfirmed pretreatment amoxicillin minimum inhibitory concentration (MIC) of greater than 256 mcg/mL by E-test and the patient was eradicated of H. pylori.

Table 1: Clarithromycin Susceptibility Test Results and Clinical/Bacteriological Outcomes [Includes only patients with pretreatment clarithromycin susceptibility test results]
Clarithromycin Pretreatment Results |  | Clarithromycin Post-treatment Results
 |  | H. pylori negative - eradicated | H. pylori positive – not eradicated Post-treatment susceptibility results
 |  |  | S [Susceptible (S) MIC ≤0.25 mcg/mL, Intermediate (I) MIC 0.5 to 1.0 mcg/mL, Resistant (R) MIC ≥2 mcg/mL] | I | R | No MIC
Triple Therapy 14-Day (lansoprazole 30 mg twice daily/amoxicillin 1 g twice daily/clarithromycin 500 mg twice daily) (M95-399, M93-131, M95-392)
Susceptible | 112 | 105 |  |  |  | 7
Intermediate | 3 | 3
Resistant | 17 | 6 |  |  | 7 | 4
Triple Therapy 10-Day (lansoprazole 30 mg twice daily/amoxicillin 1 g twice daily/clarithromycin 500 mg twice daily) (M95-399)
Susceptible | 42 | 40 | 1 |  | 1
Intermediate
Resistant | 4 | 1 |  |  | 3

Patients not eradicated of H. pylori following lansoprazole/amoxicillin/clarithromycin triple therapy will likely have clarithromycin resistant H. pylori isolates. Therefore, for those patients who fail therapy, clarithromycin susceptibility testing should be done if possible. Patients with clarithromycin resistant H. pylori should not be treated with lansoprazole/amoxicillin/clarithromycin triple therapy or other regimens which include clarithromycin as the sole antimicrobial agent.

Amoxicillin Susceptibility Test Results and Clinical/Bacteriological Outcomes

In the dual and triple therapy clinical trials, 82.6% (195/236) of the patients that had pretreatment amoxicillin susceptible MICs (≤0.25 mcg/mL) were eradicated of H. pylori. Of those with pretreatment amoxicillin MICs of greater than 0.25 mcg/mL, three of six had the H. pylori eradicated. A total of 30% (21/70) of the patients failed lansoprazole 30 mg three times daily per amoxicillin 1 g three times daily dual therapy and a total of 12.8% (22/172) of the patients failed the 10- and 14-day triple therapy regimens. Post-treatment susceptibility results were not obtained on 11 of the patients who failed therapy. Nine of the 11 patients with amoxicillin post-treatment MICs that failed the triple therapy regimen also had clarithromycin resistant H. pylori isolates.

Susceptibility Test for Helicobacter pylori

The reference methodology for susceptibility testing of H. pylori is agar dilution MICs.^1 One to three microliters of an inoculum equivalent to a No. 2 McFarland standard (1 × 10^7 – 1 × 10^8 CFU/mL for H. pylori) are inoculated directly onto freshly prepared antimicrobial containing Mueller-Hinton agar plates with 5% aged defibrinated sheep blood (≥ 2 weeks old). The agar dilution plates are incubated at 35°C in a microaerobic environment produced by a gas generating system suitable for Campylobacter species. After 3 days of incubation, the MICs are recorded as the lowest concentration of antimicrobial agent required to inhibit growth of the organism. The clarithromycin and amoxicillin MIC values should be interpreted according to the following criteria:

Clarithromycin MIC (mcg/mL) [These are tentative breakpoints for the agar dilution methodology and they should not be used to interpret results obtained using alternative methods.] | Interpretation
≤0.25 | Susceptible (S)
0.5-1.0 | Intermediate (I)
≥2.0 | Resistant (R)
Amoxicillin MIC (mcg/mL), | Interpretation
≤0.25 | Susceptible (S)

Standardized susceptibility test procedures require the use of laboratory control microorganisms to control the technical aspects of the laboratory procedures. Standard clarithromycin and amoxicillin powders should provide the following MIC values:

Microorganisms | Antimicrobial Agent | MIC (mcg/mL) [These are quality control ranges for the agar dilution methodology and they should not be used to control test results obtained using alternative methods.]
H. pylori ATCC 43504 | Clarithromycin | 0.015-0.12
H. pylori ATCC 43504 | Amoxicillin | 0.015-0.12

Antisecretory activity

After oral administration, lansoprazole was shown to significantly decrease the basal acid output and significantly increase the mean gastric pH and percent of time the gastric pH was greater than 3 and greater than 4. Lansoprazole also significantly reduced meal-stimulated gastric acid output and secretion volume, as well as pentagastrin-stimulated acid output. In patients with hypersecretion of acid, lansoprazole significantly reduced basal and pentagastrin-stimulated gastric acid secretion. Lansoprazole inhibited the normal increases in secretion volume, acidity and acid output induced by insulin.

The intragastric pH results of a five-day, pharmacodynamic, crossover study of 15 mg and 30 mg of once daily lansoprazole are presented in Table 2.

Table 2: Mean Antisecretory Effects After Single and Multiple Daily PREVACID Dosing
 |  | PREVACID
Parameter | Baseline Value | 15 mg |  | 30 mg
 |  | Day 1 | Day 5 | Day 1 | Day 5
Mean 24 Hour pH | 2.1 | 2.7 [(p<0.05) versus baseline only.] | 4.0 | 3.6 [(p<0.05) versus baseline and lansoprazole 15 mg.] | 4.9
Mean Nighttime Hour pH | 1.9 | 2.4 | 3.0 | 2.6 | 3.8
% Time Gastric pH>3 | 18 | 33 | 59 | 51 | 72
% Time Gastric pH>4 | 12 | 22 | 49 | 41 | 66
NOTE: An intragastric pH of greater than 4 reflects a reduction in gastric acid by 99%.

After the initial dose in this study, increased gastric pH was seen within 1 to 2 hours with 30 mg of lansoprazole and 2 to 3 hours with 15 mg of lansoprazole. After multiple daily dosing, increased gastric pH was seen within the first hour post-dosing with 30 mg of lansoprazole and within 1 to 2 hours post-dosing with 15 mg of lansoprazole.

Acid suppression may enhance the effect of antimicrobials in eradicating Helicobacter pylori (H. pylori). The percentage of time gastric pH was elevated above 5 and 6 was evaluated in a crossover study of PREVACID given daily, twice daily and three times daily.

Table 3: Mean Antisecretory Effects After 5 Days of Twice Daily and Three Times Daily Dosing
PREVACID
Parameter | 30 mg daily | 15 mg twice daily | 30 mg twice daily | 30 mgthree time daily
% Time Gastric pH>5 | 43 | 47 | 59 | 77 [(p<0.05) versus PREVACID 30 mg daily, 15 mg twice daily and 30 mg twice daily]
% Time Gastric pH>6 | 20 | 23 | 28 | 45

The inhibition of gastric acid secretion as measured by intragastric pH gradually returned to normal over two to four days after multiple doses. There was no indication of rebound gastric acidity.

CLINICAL STUDIES

H. pylori Eradication to Reduce the Risk of Duodenal Ulcer Recurrence

Randomized, double-blind clinical studies performed in the U.S. in patients with H. pylori and duodenal ulcer disease (defined as an active ulcer or history of an ulcer within one year) evaluated the efficacy of PREVPAC as triple 14-day therapy for the eradication of H. pylori. The triple therapy regimen (PREVACID 30 mg twice daily/amoxicillin 1 g twice daily/clarithromycin 500 mg twice daily) produced statistically significantly higher eradication rates than PREVACID plus amoxicillin, PREVACID plus clarithromycin, and amoxicillin plus clarithromycin dual therapies.

H. pylori eradication was defined as two negative tests (culture and histology) at 4 to 6 weeks following the end of treatment.

Triple therapy was shown to be more effective than all possible dual therapy combinations. The combination of PREVACID plus amoxicillin and clarithromycin as triple therapy was effective in eradicating H. pylori. Eradication of H. pylori has been shown to reduce the risk of duodenal ulcer recurrence.

A randomized, double-blind clinical study performed in the U.S. in patients with H. pylori and duodenal ulcer disease (defined as an active ulcer or history of an ulcer within one year) compared the efficacy of PREVACID triple therapy for 10 and 14 days. This study established that the 10-day triple therapy was equivalent to the 14-day triple therapy in eradicating H. pylori.

Table 4 H. pylori Eradication Rates – Triple Therapy
(PREVACID/amoxicillin/clarithromycin)
Percent of Patients Cured
[95% Confidence Interval]
(Number of patients)
Study | Duration | Triple Therapy Evaluable Analysis | Triple Therapy Intent-to-Treat Analysis
M93-131 | 14 days | 92 [(p<0.05) versus PREVACID/amoxicillin and PREVACID/clarithromycin dual therapy] [80.0-97.7] (N=48) | 86 [73.3-93.5] (N=55)
M95-392 | 14 days | 86 [(p<0.05) versus clarithromycin/amoxicillin dual therapy] [75.7-93.6] (N=66) | 83 [72.0-90.8] (N=70)
M95-399 | 14 days | 85 [77.0-91.0] (N=113) | 82 [73.9-88.1] (N=126)
 | 10 days | 84 [76.0-89.8] (N=123) | 81 [73.9-87.6] (N=135)

INDICATIONS AND USAGE

H. pylori Eradication to Reduce the Risk of Duodenal Ulcer Recurrence

The components in PREVPAC (PREVACID, amoxicillin, and clarithromycin) are indicated for the treatment of patients with H. pylori infection and duodenal ulcer disease (active or one-year history of a duodenal ulcer) to eradicate H. pylori. Eradication of H. pylori has been shown to reduce the risk of duodenal ulcer recurrence (see CLINICAL STUDIES and DOSAGE AND ADMINISTRATION).

To reduce the development of drug-resistant bacteria and maintain the effectiveness of PREVPAC and other antibacterial drugs, PREVPAC should be used only to treat or prevent infections that are proven or strongly suspected to be caused by susceptible bacteria. When culture and susceptibility information are available, they should be considered in selecting or modifying antibacterial therapy. In the absence of such data, local epidemiology and susceptibility patterns may contribute to the empiric selection of therapy.

Please refer to the full prescribing information for amoxicillin and clarithromycin.

CONTRAINDICATIONS

PREVPAC is contraindicated in patients with known severe hypersensitivity to any component of the formulation of PREVACID.

A history of allergic reaction to any of the penicillins is a contraindication.

Clarithromycin is contraindicated in patients with a known hypersensitivity to clarithromycin, erythromycin, or any of the macrolide antibiotics.

Concomitant administration of PREVPAC and any of the following drugs is contraindicated: cisapride, pimozide, astemizole, terfenadine, ergotamine or dihydroergotamine (see Drug Interactions). There have been post-marketing reports of drug interactions when clarithromycin and/or erythromycin are co-administered with cisapride, pimozide, astemizole, or terfenadine resulting in cardiac arrhythmias (QT prolongation, ventricular tachycardia, ventricular fibrillation, and torsades de pointes) most likely due to inhibition of metabolism of these drugs by erythromycin and clarithromycin. Fatalities have been reported.

For information about contraindications of other drugs that may be used in combination with amoxicillin or clarithromycin, refer to the CONTRAINDICATIONS section of their package inserts.

WARNINGS

SERIOUS AND OCCASIONALLY FATAL HYPERSENSITIVITY (ANAPHYLACTIC) REACTIONS HAVE BEEN REPORTED IN PATIENTS ON PENICILLIN THERAPY. ALTHOUGH ANAPHYLAXIS IS MORE FREQUENT FOLLOWING PARENTERAL THERAPY, IT HAS OCCURRED IN PATIENTS ON ORAL PENICILLINS. THESE REACTIONS ARE MORE LIKELY TO OCCUR IN INDIVIDUALS WITH A HISTORY OF PENICILLIN HYPERSENSITIVITY AND/OR A HISTORY OF SENSITIVITY TO MULTIPLE ALLERGENS. THERE HAVE BEEN REPORTS OF INDIVIDUALS WITH A HISTORY OF PENICILLIN HYPERSENSITIVITY WHO HAVE EXPERIENCED SEVERE REACTIONS WHEN TREATED WITH CEPHALOSPORINS. BEFORE INITIATING THERAPY WITH AMOXICILLIN, CAREFUL INQUIRY SHOULD BE MADE CONCERNING PREVIOUS HYPERSENSITIVITY REACTIONS TO PENICILLINS, CEPHALOSPORINS, OR OTHER ALLERGENS. IF AN ALLERGIC REACTION OCCURS, AMOXICILLIN SHOULD BE DISCONTINUED AND APPROPRIATE THERAPY INSTITUTED. SERIOUS ANAPHYLACTIC REACTIONS REQUIRE IMMEDIATE EMERGENCY TREATMENT WITH EPINEPHRINE. OXYGEN, INTRAVENOUS STEROIDS, AND AIRWAY MANAGEMENT, INCLUDING INTUBATION, SHOULD ALSO BE ADMINISTERED AS INDICATED.

CLARITHROMYCIN SHOULD NOT BE USED IN PREGNANT WOMEN EXCEPT IN CLINICAL CIRCUMSTANCES WHERE NO ALTERNATIVE THERAPY IS APPROPRIATE. IF PREGNANCY OCCURS WHILE TAKING CLARITHROMYCIN, THE PATIENT SHOULD BE APPRISED OF THE POTENTIAL HAZARD TO THE FETUS. CLARITHROMYCIN HAS DEMONSTRATED ADVERSE EFFECTS OF PREGNANCY OUTCOME AND/OR EMBRYO-FETAL DEVELOPMENT IN MONKEYS, RATS, MICE, AND RABBITS AT DOSES THAT PRODUCED PLASMA LEVELS 2 TO 17 TIMES THE SERUM LEVELS ACHIEVED IN HUMANS TREATED AT THE MAXIMUM RECOMMENDED HUMAN DOSES (see PRECAUTIONS - Pregnancy).

There have been post-marketing reports of colchicine toxicity with concomitant use of clarithromycin and colchicine, especially in the elderly, some of which occurred in patients with renal insufficiency. Deaths have been reported in some such patients (see PRECAUTIONS).

For information about warnings of other drugs that may be used in combination with amoxicillin or clarithromycin, refer to the WARNINGS section of their package inserts.

Clostridium difficile associated diarrhea (CDAD) has been reported with use of nearly all antibacterial agents, including clarithromycin and/or amoxicillin, and may range in severity from mild diarrhea to fatal colitis. Treatment with antibacterial agents alters the normal flora of the colon leading to overgrowth of C. difficile.

C. difficile produces toxins A and B which contribute to the development of CDAD. Hypertoxin producing strains of C. difficile cause increased morbidity and mortality, as these infections can be refractory to antimicrobial therapy and may require colectomy. CDAD must be considered in all patients who present with diarrhea following antibiotic use. Careful medical history is necessary since CDAD has been reported to occur over two months after the administration of antibacterial agents.

If CDAD is suspected or confirmed, ongoing antibiotic use not directed against C. difficile may need to be discontinued. Appropriate fluid and electrolyte management, protein supplementation, antibiotic treatment of C. difficile, and surgical evaluation should be instituted as clinically indicated.

PRECAUTIONS

Symptomatic response to therapy with PREVPAC does not preclude the presence of gastric malignancy.

The possibility of superinfections with mycotic or bacterial pathogens should be kept in mind during therapy. If superinfections occur, PREVPAC should be discontinued and appropriate therapy instituted.

Prescribing PREVPAC in the absence of a proven or strongly suspected bacterial infection or a prophylactic indication is unlikely to provide benefit to the patient and increases the risk of the development of drug-resistant bacteria.

Clarithromycin is principally excreted via the liver and kidney. Clarithromycin may be administered without dosage adjustment to patients with hepatic impairment and normal renal function. However, in the presence of severe renal impairment with or without coexisting hepatic impairment, decreased dosage or prolonged dosing intervals may be appropriate.

Exacerbation of symptoms of myasthenia gravis and new onset of symptoms of myasthenic syndrome has been reported in patients receiving clarithromycin therapy.

For information about precautions of other drugs that may be used in combination with PREVPAC, refer to the PRECAUTIONS section of their package inserts.

Information for Patients

Each dose of PREVPAC contains four pills: one pink and black capsule (PREVACID), two opaque, yellow capsules (amoxicillin) and one yellow tablet (clarithromycin). Each dose should be taken twice per day before eating. Patients should be instructed to swallow each pill whole.

PREVPAC may interact with some drugs; therefore patients should be advised to report to their doctor the use of any other medications.

Patients should be counseled that antibacterial drugs including PREVPAC should only be used to treat bacterial infections. They do not treat viral infections (e.g., the common cold). When PREVPAC is prescribed to treat a bacterial infection, patients should be told that although it is common to feel better early in the course of therapy, the medication should be taken exactly as directed. Skipping doses or not completing the full course of therapy may (1) decrease the effectiveness of the immediate treatment and (2) increase the likelihood that bacteria will develop resistance and will not be treatable by PREVPAC or other antibacterial drugs in the future.

Diarrhea is a common problem caused by antibiotics which usually ends when the antibiotic is discontinued. Sometimes after starting treatment with antibiotics, patients can develop watery and bloody stools (with or without stomach cramps and fever) even as late as two or more months after having taken the last dose of the antibiotic. If this occurs, patients should contact their physician as soon as possible.

Laboratory Tests

Amoxicillin

As with any potent drug, periodic assessment of renal, hepatic, and hematopoietic function should be made during prolonged therapy.

Drug Interactions

No drug interaction studies have been conducted specifically with PREVPAC. The following drug interactions are for the individual drug components: PREVACID (lansoprazole), amoxicillin, and clarithromycin. Therefore, the decision to adjust dosage should depend on the clinician's assessment of among other things, the cumulative or net effect of the drug components of PREVPAC.

PREVACID

PREVACID causes long-lasting inhibition of gastric acid secretion. PREVACID substantially decreases the systemic concentrations of the HIV protease inhibitor atazanavir, which is dependent upon the presence of gastric acid for absorption, and may result in a loss of therapeutic effect of atazanavir and the development of HIV resistance. Therefore, PREVACID, or other proton pump inhibitors, should not be co-administered with atazanavir.

It is theoretically possible that PREVACID may also interfere with the absorption of other drugs where gastric pH is an important determinant of bioavailability (e.g., ampicillin esters, digoxin, iron salts, ketoconazole).

PREVACID is metabolized through the cytochrome P450 system, specifically through the CYP3A and CYP2C19 isozymes. Studies have shown that PREVACID does not have clinically significant interactions with other drugs metabolized by the cytochrome P450 system, such as warfarin, antipyrine, indomethacin, ibuprofen, phenytoin, propranolol, prednisone, diazepam, or clarithromycin in healthy subjects. These compounds are metabolized through various cytochrome P450 isozymes including CYP1A2, CYP2C9, CYP2C19, CYP2D6, and CYP3A.

Theophylline

When PREVACID was administered concomitantly with theophylline (CYP1A2, CYP3A), a minor increase (10%) in the clearance of theophylline was seen. Because of the small magnitude and the direction of the effect on theophylline clearance, this interaction is unlikely to be of clinical concern. Nonetheless, individual patients may require additional titration of their theophylline dosage when PREVACID is started or stopped to ensure clinically effective blood levels.

Tacrolimus

Concomitant administration of lansoprazole and tacrolimus may increase whole blood levels of tacrolimus, especially in transplant patients who are intermediate or poor metabolizers of CYP2C19.

Warfarin

In a study of healthy subjects, neither the pharmacokinetics of warfarin enantiomers nor prothrombin time were affected following single or multiple 60 mg doses of lansoprazole. However, there have been reports of increased International Normalized Ratio (INR) and prothrombin time in patients receiving proton pump inhibitors, including PREVACID, and warfarin concomitantly. Increases in INR and prothrombin time may lead to abnormal bleeding and even death. Patients treated with proton pump inhibitors and warfarin concomitantly may need to be monitored for increases in INR and prothrombin time.

Sucralfate

In a single-dose crossover study examining PREVACID 30 mg and omeprazole 20 mg each administered alone and concomitantly with sucralfate 1 gram, absorption of the proton pump inhibitors was delayed and their bioavailability was reduced by 17% and 16%, respectively, when administered concomitantly with sucralfate. Therefore, proton pump inhibitors should be taken at least 30 minutes prior to sucralfate. In clinical trials, antacids were administered concomitantly with PREVACID and there was no evidence of a change in the efficacy of PREVACID.

Amoxicillin

Probenecid decreases the renal tubular secretion of amoxicillin. Concurrent use of amoxicillin and probenecid may result in increased and prolonged blood levels of amoxicillin.

Chloramphenicol, macrolides, sulfonamides, and tetracyclines may interfere with bactericidal effects of penicillin. This has been demonstrated in vitro; however, the clinical significance of this interaction is not well documented.

Clarithromycin

Clarithromycin use in patients who are receiving theophylline may be associated with an increase of serum theophylline concentrations. Monitoring of serum theophylline concentrations should be considered for patients receiving high doses of theophylline or with baseline concentrations in the upper therapeutic range. In two studies in which theophylline was administered with clarithromycin (a theophylline sustained-release formulation was dosed at either 6.5 mg/kg or 12 mg/kg together with 250 or 500 mg q12h clarithromycin), the steady-state levels of Cmax, Cmin, and the area under the serum concentration time curve (AUC) of theophylline increased about 20%.

Concomitant administration of single doses of clarithromycin and carbamazepine has been shown to result in increased plasma concentrations of carbamazepine. Blood level monitoring of carbamazepine may be considered.

When clarithromycin and terfenadine were coadministered, plasma concentrations of the active acid metabolite of terfenadine were threefold higher, on average, than the values observed when terfenadine was administered alone. The pharmacokinetics of clarithromycin and the 14-OH-clarithromycin were not significantly affected by coadministration of terfenadine once clarithromycin reached steady-state conditions. Concomitant administration of clarithromycin with terfenadine is contraindicated (see CONTRAINDICATIONS).

Simultaneous oral administration of clarithromycin tablets and zidovudine to HIV-infected adult patients resulted in decreased steady-state zidovudine concentrations. When 500 mg of clarithromycin were administered twice daily, steady-state zidovudine AUC was reduced by a mean of 12% (n = 4). Individual values ranged from a decrease of 34% to an increase of 14%. Based on limited data in 24 patients, when clarithromycin tablets were administered two to four hours prior to oral zidovudine, the steady-state zidovudine Cmax was increased by approximately 2-fold, whereas the AUC was unaffected.

Simultaneous administration of clarithromycin tablets and didanosine to 12 HIV-infected adult patients resulted in no statistically significant change in didanosine pharmacokinetics.

Concomitant administration of fluconazole 200 mg daily and clarithromycin 500 mg twice daily to 21 healthy volunteers led to increases in the mean steady-state clarithromycin Cmin and AUC of 33% and 18%, respectively. Steady-state concentrations of 14-OH clarithromycin were not significantly affected by concomitant administration of fluconazole.

Concomitant administration of clarithromycin and ritonavir (n = 22) resulted in a 77% increase in clarithromycin AUC and a 100% decrease in the AUC of 14-OH clarithromycin. Clarithromycin may be administered without dosage adjustment to patients with normal renal function taking ritonavir. However, for patients with renal impairment and receiving ritonavir, the dose of clarithromycin should be reduced. Refer to the clarithromycin package insert for complete information.

Spontaneous reports in the post-marketing period suggest that concomitant administration of clarithromycin and oral anticoagulants may potentiate the effects of the oral anticoagulants. Prothrombin times should be carefully monitored while patients are receiving clarithromycin and oral anticoagulants simultaneously.

Elevated digoxin serum concentrations in patients receiving clarithromycin and digoxin concomitantly have also been reported in post-marketing surveillance. Some patients have shown clinical signs consistent with digoxin toxicity, including potentially fatal arrhythmias. Serum digoxin levels should be carefully monitored while patients are receiving digoxin and clarithromycin simultaneously.

Colchicine is a substrate for both CYP3A and the efflux transporter, P-glycoprotein (Pgp). Clarithromycin and other macrolides are known to inhibit CYP3A and Pgp. When clarithromycin and colchicine are administered together, inhibition of Pgp and/or CYP3A by clarithromycin may lead to increased exposure to colchicine. Patients should be monitored for clinical symptoms of colchicine toxicity (see WARNINGS).

Erythromycin and clarithromycin are substrates and inhibitors of the 3A isoform subfamily of the cytochrome P450 enzyme system (CYP3A). Coadministration of erythromycin or clarithromycin and a drug primarily metabolized by CYP3A may be associated with elevations in drug concentrations that could increase or prolong both the therapeutic and adverse effects of the concomitant drug. Dosage adjustments may be considered, and when possible, serum concentrations of drugs primarily metabolized by CYP3A should be monitored closely in patients concurrently receiving clarithromycin or erythromycin.

The following are examples of some clinically significant CYP3A based drug interactions. Interactions with other drugs metabolized by the CYP3A isoform are also possible. Increased serum concentrations of carbamazepine and the active acid metabolite of terfenadine were observed in clinical trials with clarithromycin.

The following CYP3A based drug interactions have been observed with erythromycin products and/or with clarithromycin in post-marketing experience:

Antiarrhythmics

There have been post-marketing reports of torsades de pointes occurring with concurrent use of clarithromycin and quinidine or disopyramide. Electrocardiograms should be monitored for QTc prolongation during coadministration of clarithromycin with these drugs. Serum concentrations of these medications should also be monitored.

Ergotamine/Dihydroergotamine

Post-marketing reports indicate that coadministration of clarithromycin with ergotamine or dihydroergotamine has been associated with acute ergot toxicity characterized by vasospasm and ischemia of the extremities and other tissues including the central nervous system. Concomitant administration of clarithromycin with ergotamine or dihydroergotamine is contraindicated (see CONTRAINDICATIONS).

Triazolobenziodidiazepines (such as triazolam and alprazolam) and Related Benzodiazepines (such as midazolam)

Erythromycin has been reported to decrease the clearance of triazolam and midazolam, and thus, may increase the pharmacologic effect of these benzodiazepines. There have been postmarketing reports of drug interactions and CNS effects (e.g., somnolence and confusion) with the concomitant use of clarithromycin and triazolam.

HMG-CoA Reductase Inhibitors

As with other macrolides, clarithromycin has been reported to increase concentrations of HMG-CoA reductase inhibitors (e.g., lovastatin and simvastatin). Rare reports of rhabdomyolysis have been reported in patients taking these drugs concomitantly.

Sildenafil (Viagra)

Erythromycin has been reported to increase the systemic exposure (AUC) of sildenafil. A similar interaction may occur with clarithromycin; reduction of sildenafil dosage should be considered (see Viagra package insert).

There have been spontaneous or published reports of CYP3A based interactions of erythromycin and/or clarithromycin with cyclosporine, carbamazepine, tacrolimus, alfentanil, disopyramide, rifabutin, quinidine, methylprednisolone, cilostazol, and bromocriptine.

Concomitant administration of clarithromycin with cisapride, pimozide, astemizole, or terfenadine is contraindicated (see CONTRAINDICATIONS).

In addition, there have been reports of interactions of erythromycin or clarithromycin with drugs not thought to be metabolized by CYP3A, including hexobarbital, phenytoin, and valproate.

Drug/Laboratory Test Interactions

High urine concentrations of ampicillin may result in false-positive reactions when testing for the presence of glucose in urine using CLINITEST®, Benedict's Solution or Fehling's Solution. Since this effect may also occur with amoxicillin, it is recommended that glucose tests based on enzymatic glucose oxidase reactions (such as CLINISTIX®) be used.

Following administration of ampicillin to pregnant women, a transient decrease in plasma concentration of total conjugated estriol, estriol-glucuronide, conjugated estrone, and estradiol has been noted. This effect may also occur with amoxicillin.

Carcinogenesis, Mutagenesis, Impairment of Fertility

In two 24-month carcinogenicity studies, Sprague-Dawley rats were treated with oral lansoprazole doses of 5 to 150 mg/kg/day, about 1 to 40 times the exposure on a body surface (mg/m^2) basis of a 50 kg person of average height [1.46 m^2 body surface area (BSA)] given the recommended human dose of 30 mg/day. Lansoprazole produced dose-related gastric enterochromaffin-like (ECL) cell hyperplasia and ECL cell carcinoids in both male and female rats. It also increased the incidence of intestinal metaplasia of the gastric epithelium in both sexes. In male rats, lansoprazole produced a dose-related increase of testicular interstitial cell adenomas. The incidence of these adenomas in rats receiving doses of 15 to 150 mg/kg/day (4 to 40 times the recommended human dose based on BSA) exceeded the low background incidence (range = 1.4 to 10%) for this strain of rat.

In a 24-month carcinogenicity study, CD-1 mice were treated with oral lansoprazole doses of 15 to 600 mg/kg/day, 2 to 80 times the recommended human dose based on BSA. Lansoprazole produced a dose-related increased incidence of gastric ECL cell hyperplasia. It also produced an increased incidence of liver tumors (hepatocellular adenoma plus carcinoma). The tumor incidences in male mice treated with 300 and 600 mg/kg/day (40 to 80 times the recommended human dose based on BSA) and female mice treated with 150 to 600 mg/kg/day (20 to 80 times the recommended human dose based on BSA) exceeded the ranges of background incidences in historical controls for this strain of mice. Lansoprazole treatment produced adenoma of rete testis in male mice receiving 75 to 600 mg/kg/day (10 to 80 times the recommended human dose based on BSA).

A 26 week p53 (+/-) transgenic mouse carcinogenicity study was not positive.

Lansoprazole was not genotoxic in the Ames test, the ex vivo rat hepatocyte unscheduled DNA synthesis (UDS) test, the in vivo mouse micronucleus test, or the rat bone marrow cell chromosomal aberration test. It was positive in in vitro human lymphocyte chromosomal aberration assays.

Lansoprazole at oral doses up to 150 mg/kg/day (40 times the recommended human dose based on BSA) was found to have no effect on fertility and reproductive performance of male and female rats.

Long-term studies in animals have not been performed to evaluate carcinogenic potential. Studies to detect mutagenic potential of amoxicillin alone have not been conducted; however, the following information is available from tests on a 4:1 mixture of amoxicillin and potassium clavulanate. Amoxicillin and potassium clavulanate was non-mutagenic in the Ames bacterial mutation assay, and the yeast gene conversion assay. Amoxicillin and potassium clavulanate was weakly positive in the mouse lymphoma assay, but the trend toward increased mutation frequencies in this assay occurred at doses that were also associated with decreased cell survival. Amoxicillin and potassium clavulanate was negative in the mouse micronucleus test, and in the dominant lethal assay in mice. Potassium clavulanate alone was tested in the Ames bacterial mutation assay and in the mouse micronucleus test, and was negative in each of these assays. In a multi-generation reproduction study in rats, no impairment of fertility or other adverse reproductive effects were seen at doses up to 500 mg/kg (approximately 3 times the human dose in mg/m^2).

The following in vitro mutagenicity tests have been conducted with clarithromycin:

Salmonella/Mammalian Microsomes Test

Bacterial Induced Mutation Frequency Test

In Vitro Chromosome Aberration Test

Rat Hepatocyte DNA Synthesis Assay

Mouse Lymphoma Assay

Mouse Dominant Lethal Study

Mouse Micronucleus Test

All tests had negative results except the In Vitro Chromosome Aberration Test which was weakly positive in one test and negative in another.

In addition, a Bacterial Reverse-Mutation Test (Ames Test) has been performed on clarithromycin metabolites with negative results.

Fertility and reproduction studies have shown that daily doses of up to 160 mg/kg/day (1.3 times the recommended maximum human dose based on mg/m^2) to male and female rats caused no adverse effects on the estrous cycle, fertility, parturition, or number and viability of offspring. Plasma levels in rats after 150 mg/kg/day were 2 times the human serum levels.

In the 150 mg/kg/day monkey studies, plasma levels were 3 times the human serum levels. When given orally at 150 mg/kg/day (2.4 times the recommended maximum human dose based on mg/m^2), clarithromycin was shown to produce embryonic loss in monkeys. This effect has been attributed to marked maternal toxicity of the drug at this high dose.

In rabbits, in utero fetal loss occurred at an intravenous dose of 33 mg/m^2, which is 17 times less than the maximum proposed human oral daily dose of 618 mg/m^2.

Long-term studies in animals have not been performed to evaluate the carcinogenic potential of clarithromycin.

Pregnancy

Teratogenic Effects

Pregnancy Category C

Category C is based on the pregnancy category for clarithromycin.

Four teratogenicity studies in rats (three with oral doses and one with intravenous doses up to 160 mg/kg/day administered during the period of major organogenesis) and two in rabbits at oral doses up to 125 mg/kg/day (approximately 2 times the recommended maximum human dose based on mg/m^2) or intravenous doses of 30 mg/kg/day administered during gestation days 6 to 18 failed to demonstrate any teratogenicity from clarithromycin. Two additional oral studies in a different rat strain at similar doses and similar conditions demonstrated a low incidence of cardiovascular anomalies at doses of 150 mg/kg/day administered during gestation days 6 to 15. Plasma levels after 150 mg/kg/day were 2 times the human serum levels. Four studies in mice revealed a variable incidence of cleft palate following oral doses of 1000 mg/kg/day (2 and 4 times the recommended maximum human dose based on mg/m^2, respectively) during gestation days 6 to 15. Cleft palate was also seen at 500 mg/kg/day. The 1000 mg/kg/day exposure resulted in plasma levels 17 times the human serum levels. In monkeys, an oral dose of 70 mg/kg/day (an approximate equidose of the recommended maximum human dose based on mg/m^2) produced fetal growth retardation at plasma levels that were 2 times the human serum levels.

There were no adequate and well-controlled studies of PREVPAC in pregnant women. PREVPAC should be used during pregnancy only if the potential benefit justifies the potential risk to the fetus (see WARNINGS).

Labor and Delivery

Oral ampicillin-class antibiotics are poorly absorbed during labor. Studies in guinea pigs showed that intravenous administration of ampicillin slightly decreased the uterine tone and frequency of contractions, but moderately increased the height and duration of contractions. However, it is not known whether use of these drugs in humans during labor or delivery has immediate or delayed adverse effects on the fetus, prolongs the duration of labor, or increases the likelihood that forceps delivery or other obstetrical intervention or resuscitation of the newborn will be necessary.

Nursing Mothers

Lansoprazole or its metabolites are excreted in the milk of rats. It is not known whether lansoprazole is excreted in human milk.

Penicillins have been shown to be excreted in human milk. Amoxicillin use by nursing mothers may lead to sensitization of infants. Caution should be exercised when amoxicillin is administered to a nursing woman.

It is not known whether clarithromycin is excreted in human milk. It is known that clarithromycin is excreted in the milk of lactating animals and that other drugs of this class are excreted in human milk.

Due to the potential for serious adverse reactions in nursing infants from PREVPAC, and the potential for tumorigenicity shown for lansoprazole in rat carcinogenicity studies, a decision should be made whether to discontinue nursing or to discontinue PREVPAC, taking into account the importance of the therapy to the mother.

Pediatric Use

The safety and effectiveness of PREVPAC in pediatric patients infected with H. pylori have not been established (see CONTRAINDICATIONS and WARNINGS).

Geriatric Use

Elderly patients may suffer from asymptomatic renal and hepatic dysfunction. Care should be taken when administering PREVPAC to this patient population.

An analysis of clinical studies of amoxicillin was conducted to determine whether subjects aged 65 and over respond differently from younger subjects. Of the 1,811 subjects treated with capsules of amoxicillin, 85% were less than 60 years old, 15% were ≥ 61 years old and 7% were ≥ 71 years old. This analysis and other reported clinical experience have not identified differences in responses between the elderly and younger patients, but a greater sensitivity of some older individuals cannot be ruled out.

This drug is known to be substantially excreted by the kidney, and the risk of toxic reactions to this drug may be greater in patients with impaired renal function. Because elderly patients are more likely to have decreased renal function, care should be taken in dose selection, and it may be useful to monitor renal function.

In a steady-state study in which healthy elderly subjects (age 65 to 81 years old) were given 500 mg every 12 hours, the maximum serum concentrations and area under the curves of clarithromycin and 14-OH clarithromycin were increased compared to those achieved in healthy young adults. These changes in pharmacokinetics parallel known age-related decreases in renal function. In clinical trials, elderly patients did not have an increased incidence of adverse events when compared to younger patients. Dosage adjustment should be considered in elderly patients with severe renal impairment (see WARNINGS and PRECAUTIONS).

ADVERSE REACTIONS

The most common adverse reactions (≥3%) reported in clinical trials when all three components of this therapy were given concomitantly for 14 days are listed in Table 5.

Table 5: Adverse Reactions Most Frequently Reported in Clinical Trials (≥ 3%)
 | Triple Therapy
 | n=138
Adverse Reaction | (%)
Diarrhea | 7.0
Headache | 6.0
Taste Perversion | 5.0

The additional adverse reactions which were reported as possibly or probably related to treatment (less than 3%) in clinical trials when all three components of this therapy were given concomitantly are listed below and divided by body system:

Body as a Whole - abdominal pain
Digestive System - dark stools, dry mouth/thirst, glossitis, rectal itching, nausea, oral moniliasis, stomatitis, tongue discoloration, tongue disorder, vomiting
Musculoskeletal System - myalgia
Nervous System - confusion, dizziness
Respiratory System - respiratory disorders
Skin and Appendages - skin reactions
Urogenital System - vaginitis, vaginal moniliasis.

There were no statistically significant differences in the frequency of reported adverse events between the 10- and 14-day triple therapy regimens.

The following adverse reactions from the labeling for PREVACID are provided for information:

Worldwide, over 10,000 patients have been treated with PREVACID in Phase 2 or Phase 3 clinical trials involving various dosages and durations of treatment. In general, PREVACID treatment has been well-tolerated in both short-term and long-term trials.

Incidence in Clinical Trials

The following adverse events were reported by the treating physician to have a possible or probable relationship to drug in 1% or more of PREVACID-treated patients and occurred at a greater rate in PREVACID-treated patients than placebo-treated patients:

Table 6: Incidence of Possibly or Probably Treatment-Related Adverse Reactions in Short-Term, Placebo-Controlled PREVACID Studies
 | PREVACID | Placebo
Body System/Adverse Event | (N= 2768) | (N= 1023)
 | % | %
Body as a Whole
Abdominal Pain | 2.1 | 1.2
Digestive System
Constipation | 1.0 | 0.4
Diarrhea | 3.8 | 2.3
Nausea | 1.3 | 1.2

Headache was also seen at greater than 1% incidence but was more common on placebo. The incidence of diarrhea was similar between patients who received placebo and patients who received 15 mg and 30 mg of PREVACID, but higher in the patients who received 60 mg of PREVACID (2.9%, 1.4%, 4.2%, and 7.4%, respectively).

The most commonly reported possibly or probably treatment-related adverse event during maintenance therapy was diarrhea.

Additional adverse experiences occurring in less than 1% of patients or subjects who received PREVACID in domestic trials are shown below:

Body as a Whole – abdomen enlarged, allergic reaction, asthenia, back pain, candidiasis, carcinoma, chest pain (not otherwise specified), chills, edema, fever, flu syndrome, halitosis, infection (not otherwise specified), malaise, neck pain, neck rigidity, pain, pelvic pain

Cardiovascular System – angina, arrhythmia, bradycardia, cerebrovascular accident/cerebral infarction, hypertension/hypotension, migraine, myocardial infarction, palpitations, shock (circulatory failure), syncope, tachycardia, vasodilation

Digestive System – abnormal stools, anorexia, bezoar, cardiospasm, cholelithiasis, colitis, dry mouth, dyspepsia, dysphagia, enteritis, eructation, esophageal stenosis, esophageal ulcer, esophagitis, fecal discoloration, flatulence, gastric nodules/fundic gland polyps, gastritis, gastroenteritis, gastrointestinal anomaly, gastrointestinal disorder, gastrointestinal hemorrhage, glossitis, gum hemorrhage, hematemesis, increased appetite, increased salivation, melena, mouth ulceration, nausea and vomiting, nausea and vomiting and diarrhea, gastrointestinal moniliasis, rectal disorder, rectal hemorrhage, stomatitis, tenesmus, thirst, tongue disorder, ulcerative colitis, ulcerative stomatitis

Endocrine System – diabetes mellitus, goiter, hypothyroidism

Hemic and Lymphatic System – anemia, hemolysis, lymphadenopathy

Metabolic and Nutritional Disorders – avitaminosis, gout, dehydration, hyperglycemia/hypoglycemia, peripheral edema, weight gain/loss

Musculoskeletal System – arthralgia, arthritis, bone disorder, joint disorder, leg cramps, musculoskeletal pain, myalgia, myasthenia, ptosis, synovitis

Nervous System – abnormal dreams, agitation, amnesia, anxiety, apathy, confusion, convulsion, dementia, depersonalization, depression, diplopia, dizziness, emotional lability, hallucinations, hemiplegia, hostility aggravated, hyperkinesia, hypertonia, hypesthesia, insomnia, libido decreased/increased, nervousness, neurosis, paresthesia, sleep disorder, somnolence, thinking abnormality, tremor, vertigo

Respiratory System – asthma, bronchitis, cough increased, dyspnea, epistaxis, hemoptysis, hiccup, laryngeal neoplasia, lung fibrosis, pharyngitis, pleural disorder, pneumonia, respiratory disorder, upper respiratory inflammation/infection, rhinitis, sinusitis, stridor

Skin and Appendages – acne, alopecia, contact dermatitis, dry skin, fixed eruption, hair disorder, maculopapular rash, nail disorder, pruritus, rash, skin carcinoma, skin disorder, sweating, urticaria

Special Senses – abnormal vision, amblyopia, blepharitis, blurred vision, cataract, conjunctivitis, deafness, dry eyes, ear/eye disorder, eye pain, glaucoma, otitis media, parosmia, photophobia, retinal degeneration/disorder, taste loss, taste perversion, tinnitus, visual field defect

Urogenital System – abnormal menses, breast enlargement, breast pain, breast tenderness, dysmenorrhea, dysuria, gynecomastia, impotence, kidney calculus, kidney pain, leukorrhea, menorrhagia, menstrual disorder, penis disorder, polyuria, testis disorder, urethral pain, urinary frequency, urinary retention, urinary tract infection, urinary urgency, urination impaired, vaginitis

Postmarketing

Additional adverse experiences have been reported since PREVACID has been marketed. The majority of these cases are foreign-sourced and a relationship to PREVACID has not been established. Because these events were reported voluntarily from a population of unknown size, estimates of frequency cannot be made. These events are listed below by COSTART body system:

Body as a Whole – anaphylactic/anaphylactoid reactions

Digestive System – hepatotoxicity, pancreatitis, vomiting

Hemic and Lymphatic System – agranulocytosis, aplastic anemia, hemolytic anemia, leukopenia, neutropenia, pancytopenia, thrombocytopenia, and thrombotic thrombocytopenic purpura

Musculoskeletal System – myositis

Skin and Appendages – severe dermatologic reactions including erythema multiforme, Stevens-Johnson syndrome, toxic epidermal necrolysis, (some fatal)

Special Senses – speech disorder

Urogenital System – interstitial nephritis, urinary retention

Laboratory Values

The following changes in laboratory parameters in patients who received PREVACID were reported as adverse events:

Abnormal liver function tests, increased SGOT (AST), increased SGPT (ALT), increased creatinine, increased alkaline phosphatase, increased globulins, increased GGTP, increased/decreased/abnormal WBC, abnormal AG ratio, abnormal RBC, bilirubinemia, blood potassium increased, blood urea increased, crystal urine present, eosinophilia, hemoglobin decreased, hyperlipemia, increased/decreased electrolytes, increased/decreased cholesterol, increased glucocorticoids, increased LDH, increased/decreased/abnormal platelets, increased gastrin levels and positive fecal occult blood. Urine abnormalities such as albuminuria, glycosuria, and hematuria were also reported. Additional isolated laboratory abnormalities were reported.

In the placebo-controlled studies, when SGOT (AST) and SGPT (ALT) were evaluated, 0.4% (4/978) and 0.4% (11/2677) patients, who received placebo and PREVACID, respectively, had enzyme elevations greater than three times the upper limit of normal range at the final treatment visit. None of these patients who received PREVACID reported jaundice at any time during the study.

The following adverse reactions from the labeling for amoxicillin are provided for information:

As with other penicillins, it may be expected that untoward reactions will be essentially limited to sensitivity phenomena. They are more likely to occur in individuals who have previously demonstrated hypersensitivity to penicillins and in those with a history of allergy, asthma, hay fever, or urticaria.

The following adverse reactions have been reported as associated with the use of penicillins:

Gastrointestinal - Nausea, vomiting, diarrhea, and hemorrhagic/pseudomembranous colitis.

Onset of pseudomembranous colitis symptoms may occur during or after antibiotic treatment (see WARNINGS).

Hypersensitivity Reactions – Serum sickness-like reactions, erythematous maculopapular rashes, erythema multiforme, Stevens-Johnson Syndrome, exfoliative dermatitis, toxic epidermal necrolysis, acute generalized exanthematous pustulosis, hypersensitivity vasculitis and urticaria have been reported.

Note: These hypersensitivity reactions may be controlled with antihistamines and, if necessary, systemic corticosteroids. Whenever such reactions occur, amoxicillin should be discontinued unless, in the opinion of the physician, the condition being treated is life-threatening and amenable only to amoxicillin therapy.

Liver – A moderate rise in AST (SGOT) and/or ALT (SGPT) has been noted, but the significance of this finding is unknown. Hepatic dysfunction including cholestatic jaundice, hepatic cholestasis and acute cytolytic hepatitis have been reported.

Renal – Crystalluria has also been reported (see OVERDOSAGE).

Hemic and Lymphatic Systems – Anemia, including hemolytic anemia, thrombocytopenia, thrombocytopenic purpura, eosinophilia, leukopenia and agranulocytosis have been reported during therapy with penicillins. These reactions are usually reversible on discontinuation of therapy and are believed to be hypersensitivity phenomena.

Central Nervous System – Reversible hyperactivity, agitation, anxiety, insomnia, confusion, behavioral changes, and/or dizziness have been reported rarely.

Miscellaneous – Tooth discoloration (brown, yellow, or gray staining) has been rarely reported. Most reports occurred in pediatric patients. Discoloration was reduced or eliminated with brushing or dental cleaning in most cases.

The following adverse reactions from the labeling for clarithromycin are provided for information.

The majority of side effects observed in clinical trials were of a mild and transient nature. Fewer than 3% of adult patients without mycobacterial infections discontinued therapy because of drug-related side effects.

The most frequently reported events in adults were diarrhea (3%), nausea (3%), abnormal taste (3%), dyspepsia (2%), abdominal pain/discomfort (2%), and headache (2%). Most of these events were described as mild or moderate in severity. Of the reported adverse events, only 1% was described as severe.

Postmarketing Experience

Allergic reactions ranging from urticaria and mild skin eruptions to rare cases of anaphylaxis, Stevens-Johnson syndrome, and toxic epidermal necrolysis have occurred. Other spontaneously reported adverse events include glossitis, stomatitis, oral moniliasis, anorexia, vomiting, pancreatitis, tongue discoloration, thrombocytopenia, leukopenia, neutropenia, and dizziness. There have been reports of tooth discoloration in patients treated with clarithromycin. Tooth discoloration is usually reversible with professional dental cleaning. There have been isolated reports of hearing loss, which is usually reversible, occurring chiefly in elderly women. Reports of alterations of the sense of smell including smell loss, usually in conjunction with taste perversion or taste loss have also been reported.

Transient CNS events including anxiety, behavioral changes, confusional states, convulsions, depersonalization, disorientation, hallucinations, insomnia, manic behavior, nightmares, psychosis, tinnitus, tremor, and vertigo have been reported during postmarketing surveillance. Events usually resolve with discontinuation of the drug.

Hepatic dysfunction, including increased liver enzymes, and hepatocellular and/or cholestatic hepatitis, with or without jaundice, has been infrequently reported with clarithromycin. This hepatic dysfunction may be severe and is usually reversible. In very rare instances, hepatic failure with fatal outcome has been reported and generally has been associated with serious underlying diseases and/or concomitant medications.

There have been rare reports of hypoglycemia, some of which have occurred in patients taking oral hypoglycemic agents or insulin.

As with other macrolides, clarithromycin has been associated with QT prolongation and ventricular arrhythmias, including ventricular tachycardia and torsades de pointes.

There have been reports of interstitial nephritis coincident with clarithromycin use.

There have been post-marketing reports of colchicine toxicity with concomitant use of clarithromycin and colchicine, especially in the elderly, some of which occurred in patients with renal insufficiency. Deaths have been reported in some such patients (see WARNINGS and PRECAUTIONS).

Changes in laboratory values with possible clinical significance were as follows: Hepatic – elevated SGPT (ALT) less than 1%, SGOT (AST) less than 1%, GGT less than 1%, alkaline phosphatase less than 1%, LDH less than 1%, total bilirubin less than 1%; Hematologic – decreased WBC less than 1%, elevated prothrombin time 1%; Renal – elevated BUN 4%, elevated serum creatinine less than 1%. GGT, alkaline phosphatase, and prothrombin time data are from adult studies only.

OVERDOSAGE

In case of an overdose, patients should contact a physician, poison control center, or emergency room. There is neither a pharmacologic basis nor data suggesting an increased toxicity of the combination compared to individual components.

PREVACID is not removed from the circulation by hemodialysis. In one reported overdose, a patient consumed 600 mg of PREVACID with no adverse reaction.Oral PREVACID doses up to 5000 mg/kg in rats [approximately 1300 times the 30 mg human dose based on (BSA)] and in mice (about 675.7 times the 30 mg human dose based on BSA) did not produce deaths or any clinical signs.

In case of overdosage, discontinue medication, treat symptomatically and institute supportive measures as required. If the overdosage is very recent and there is no contraindication, an attempt at emesis or other means of removal of drug from the stomach may be performed. A prospective study of 51 pediatric patients at a poison-control center suggested that overdosages of less than 250 mg/kg of amoxicillin are not associated with significant clinical symptoms and do not require gastric emptying.^2

Interstitial nephritis resulting in oliguric renal failure has been reported in a small number of patients after overdosage with amoxicillin.

Crystalluria, in some cases leading to renal failure, has also been reported after amoxicillin overdosage in adult and pediatric patients. In case of overdosage, adequate fluid intake and diuresis should be maintained to reduce the risk of amoxicillin crystalluria. Renal impairment appears to be reversible with cessation of drug administration. High blood levels may occur more readily in patients with impaired renal function because of decreased renal clearance of amoxicillin. Amoxicillin can be removed from circulation by hemodialysis.

Overdosage of clarithromycin can cause gastrointestinal symptoms such as abdominal pain, vomiting, nausea, and diarrhea.

Adverse reactions accompanying overdosage should be treated by the prompt elimination of unabsorbed drug and supportive measures. As with other macrolides, clarithromycin serum levels are not expected to be appreciably affected by hemodialysis or peritoneal dialysis.

DOSAGE AND ADMINISTRATION

H. pylori Eradication to Reduce the Risk of Duodenal Ulcer Recurrence

The recommended adult oral dose is 30 mg PREVACID, 1 g amoxicillin, and 500 mg clarithromycin administered together twice daily (morning and evening) for 10 or 14 days (see INDICATIONS AND USAGE).

PREVPAC is not recommended in patients with creatinine clearance less than 30 mL/min.

HOW SUPPLIED

PREVPAC is supplied as an individual daily administration card, each containing:

PREVACID:

–Two opaque, hard gelatin, black and pink PREVACID 30-mg capsules, with "TAP" and "PREVACID 30" imprinted on the capsules.

Amoxicillin Capsules, USP:

–Four yellow, opaque, hard gelatin amoxicillin 500-mg capsules, USP, imprinted AMOX 500 on one side and GG 849 on the other side.

BIAXIN Filmtab:

–Two yellow oval film-coated clarithromycin 500-mg tablets, USP, debossed with the Abbott logo on one side and "KL" on the other side of the tablets.

NDC 54868-4909-0 Carton containing 14 daily administration cards

Store between 20°C and 25°C (68°F and 77°F)[see USP Controlled Room Temperature]. Protect from light and moisture.

Rx only

REFERENCE

1. National Committee for Clinical Laboratory Standards. Summary Minutes, Subcommittee on Antimicrobial Susceptibility Testing, Tampa, FL, January 11-13, 1998.
2. Swanson Biearman B, Dean BS, Lopez G, Krenzelok EP. The effects of penicillin and cephalosporin ingestions in children less than six years of age. Vet Hum Toxicol. 1988; 30:66-67.

U.S. Patent No. 5,013,743

PREVPAC is distributed by Takeda Pharmaceuticals America, Inc.

PREVACID® (lansoprazole) Delayed-Release Capsules
Distributed by Takeda Pharmaceuticals America, Inc.
Deerfield, IL 60015, U.S.A.

Amoxicillin Capsules, USP
Manufactured in Austria by Sandoz GmbH
for Sandoz Inc., Princeton, NJ 08540, U.S.A.

BIAXIN® Filmtab® (clarithromycin tablets, USP)
Manufactured by Abbott Pharmaceuticals PR, Ltd.
Barceloneta, PR 00617

PREVACID® and PREVPAC® are registered trademarks of Takeda Pharmaceuticals North America, Inc. and used under license by Takeda Pharmaceuticals America, Inc.

All other trademark names are the property of their respective owners.

© 1997-2009 Takeda Pharmaceuticals America, Inc.

PAC0909 R14, October 2009

Relabeling of "Additional Barcode Label" by:

Physicians Total Care, Inc.
Tulsa, OK 74146

PRINCIPAL DISPLAY PANEL - Carton

triple therapy
PREVPAC®
LANSOPRAZOLE
AMOXICILLIN
CLARITHROMYCIN

14 DAILY PATIENT CARDS

EACH DAILY PATIENT
CARD CONTAINS:
2 PREVACID® (lansoprazole) 30-mg capsules;
4 AMOXICILLIN CAPSULES, USP, 500 mg; and
2 BIAXIN® Filmtab® (clarithromycin tablets, USP) 500 mg

Rx only